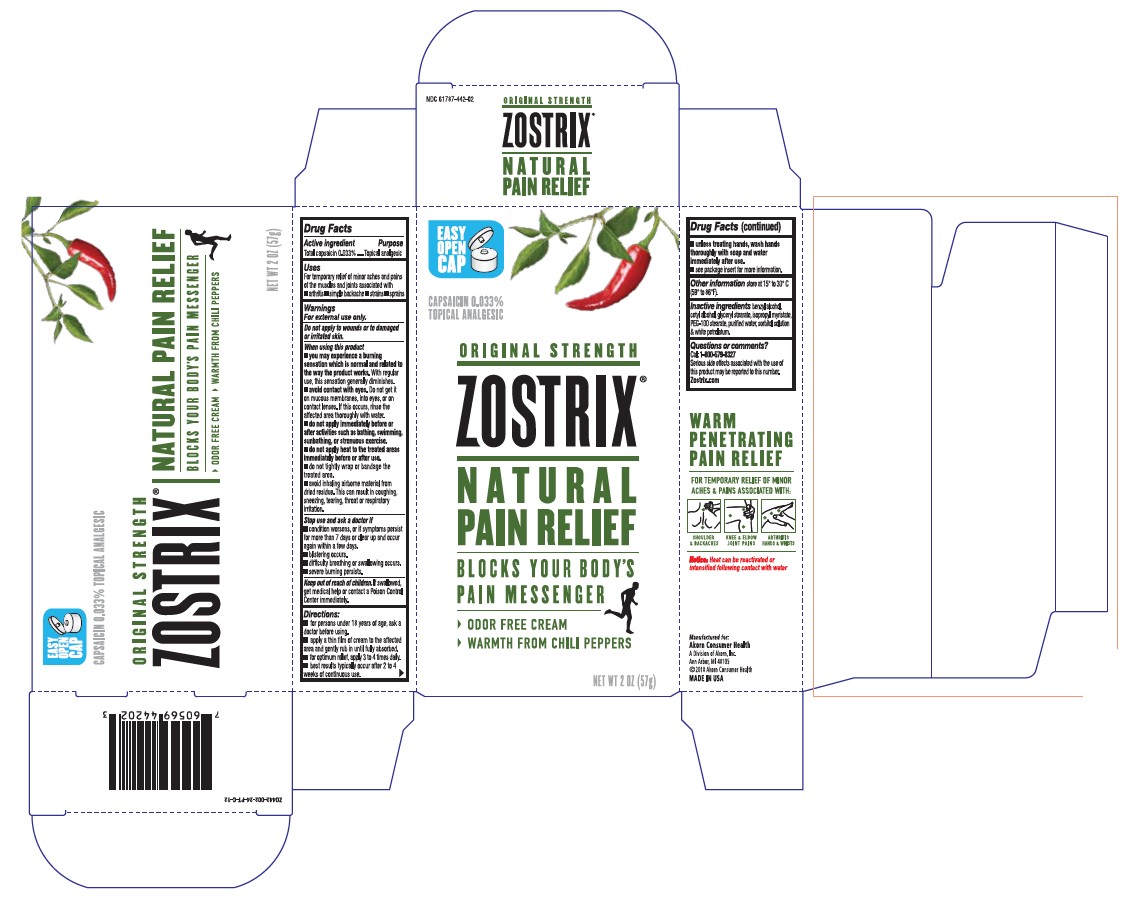 DRUG LABEL: Zostrix Original Strength
NDC: 61787-442 | Form: CREAM
Manufacturer: Akorn Consumer Health
Category: otc | Type: HUMAN OTC DRUG LABEL
Date: 20201217

ACTIVE INGREDIENTS: CAPSAICIN .25 mg/1 g
INACTIVE INGREDIENTS: BENZYL ALCOHOL; CETYL ALCOHOL; GLYCERYL MONOSTEARATE; ISOPROPYL MYRISTATE; PEG-100 STEARATE; WATER; SORBITOL; PETROLATUM

Drug Facts

Active ingredient

Capsaicin 0.025%

Purpose

Topical Analgesic

Keep Out of Reach of Children

If swallowed, get medical help or contact a PoisonControlCenter immediately.

Uses

- for the temporary relief of minor aches and pains of muscles and joints associated with arthritis, simple backache, strains and sprains

Warnings

For external use only.

Do not apply to wounds or to damaged or irritated skin.

When using this product

- you may experience a burning sensation which is normal and related to the way the product works. With regular use, this sensation generally disappears within several days.
- avoid contact with eyes. Do not get it on mucous membranes, into eyes, or on contact lenses. If this occurs, rinse the affected area thoroughly with water.
- do not apply immediately before or after activities such as bathing, swimming, sun bathing, or strenuous exercise
- do not apply heat to the treated areas immediately before or after use
- do not tightly wrap or bandage the treated area
- avoid inhaling airborne material from dried residue. This can result in coughing, sneezing, tearing, throat or respiratory irritation.

Stop use and ask a doctor if

- condition worsens, or if symptoms persist for more than 7 days or clear up and occur again within a few days, discontinue use of this product and consult a doctor
- blistering occurs
- difficulty breathing or swallowing occurs
- severe burning persists

Directions

- for persons under 18 years of age, ask a doctor before using
- apply a thin film of cream and gently rub in until fully absorbed
- for optimum relief, apply 3 to 4 times daily
- best results typically occur after 2 to 4 weeks of continuous use
- unless treating hands, wash hands thoroughly with soap and water immediately after use
- see package insert for more information

Other information

Store at 15°-30°C (59°-86°F)

Inactive Ingredients

benzyl alcohol, cetyl alcohol, glyceryl stearate, isopropyl myristate, PEG-100 stearate, purified water, sorbitol solution & white petrolatum.

Questions or Comments?

Call: 1-866-263-9003, Mon-Thurs 9:00 am - 5:00 pm EST, Fri 9:00 am - 2:30 pm EST. Serious side effects associated with use of this product may be reported to this number.

Package/Label Principal Display Panel

NDC 61787-442-02

CAPSAICIN 0.033%

TOPICAL ANALGESIC

ORIGINAL STRENGTH

ZOSTRIX

NATURAL PAIN RELIEF

BLOCKS YOUR BODY’S

PAIN MESSENGER

- ODOR FREE CREAM
- WARMTH FROM CHILI PEPPERS

NET WT 2 OZ (57 g)